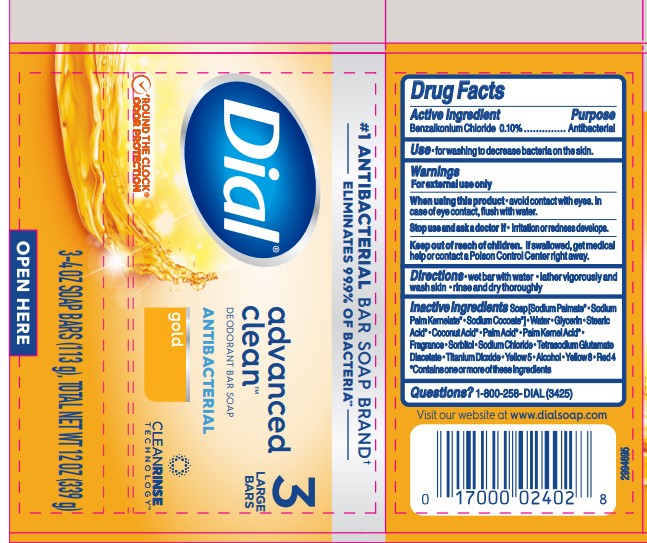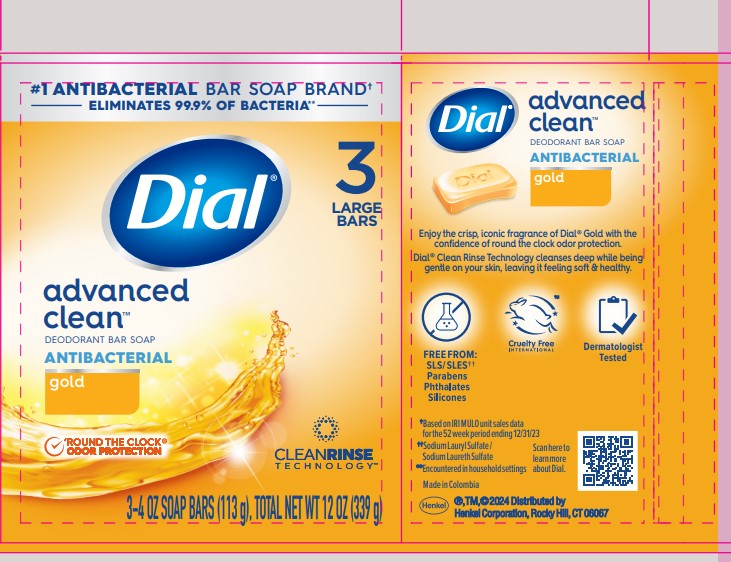 DRUG LABEL: Dial Antibacterial Bar
NDC: 54340-272 | Form: SOAP
Manufacturer: Henkel Corporation
Category: otc | Type: HUMAN OTC DRUG LABEL
Date: 20251113

ACTIVE INGREDIENTS: BENZALKONIUM CHLORIDE 0.1 g/100 g
INACTIVE INGREDIENTS: EXT. D&C YELLOW NO. 7; GLYCERIN 8.1 g/100 g; WATER 14.086 g/100 g; SODIUM CHLORIDE 0.393 g/100 g; SODIUM PALM KERNELATE 11.07 g/100 g; SORBITOL 0.652 g/100 g; FD&C YELLOW NO. 5 0.0182 g/100 g; TETRASODIUM GLUTAMATE DIACETATE 0.0588 g/100 g; STEARIC ACID 2.45 g/100 g; TITANIUM DIOXIDE 0.035 g/100 g; ALCOHOL 0.01 g/100 g; CI 14700

Dial Antibacterial Bar Soap - Gold
Dial Gold Antibacterial Deodorant Bar
Dial Advanced Clean Deodorant Bar Soap Antibacterial Gold

Active ingredient

Benzalkonium Chloride 0.10%

Purpose

Antibacterial

Uses

• for washing to decrease the bacterial on the skin

Warnings

For external use only

When using this product

• avoid contact with eyes. In case of eye contact, flush with water.

Stop using and ask doctor if

• irritation or redness develops

Keep out of reach of children.

If swallowed, get medical help or contact a Poison Control Center right away.

Directions

• wet bar with water
• lather vigorously and wash skin
• rinse and dry thoroughly

Inactive ingredients:

Soap [Sodium Palmate* · Sodium Cocoate* · Sodium Palm Kernelate*] · Water · Glycerin · Coconut Acid* · Palm Acid* · Palm Kernel Acid* · Stearic Acid* · Fragrance · Sorbitol · Sodium Chloride · Tetrasodium Glutamate Diacetate · Titanium Dioxide · Yellow 5 · Alcohol · Yellow 8 · Red 4
*Contains one or more of these ingredients